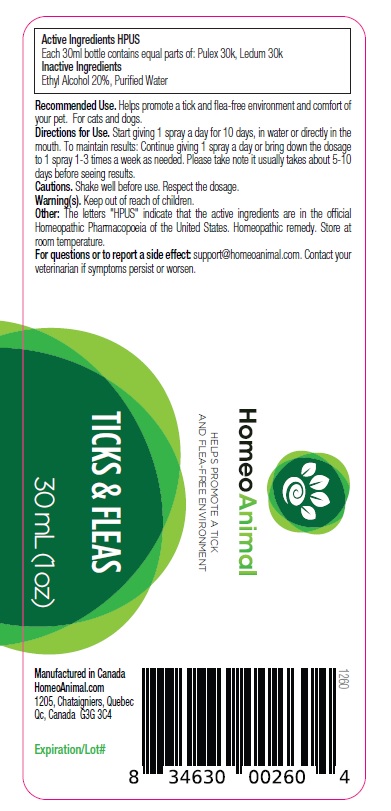 DRUG LABEL: TICKS and FLEAS
NDC: 86147-058 | Form: LIQUID
Manufacturer: Groupe Cyrenne Inc.
Category: homeopathic | Type: OTC ANIMAL DRUG LABEL
Date: 20230419

ACTIVE INGREDIENTS: PULEX IRRITANS 30 [kp_C]/30 mL; RHODODENDRON TOMENTOSUM LEAFY TWIG 30 [kp_C]/30 mL
INACTIVE INGREDIENTS: ALCOHOL; WATER

Active ingredients

pulex 30k, ledum 30k

Uses

Helps promote a tick and flea-free environment and comfort of your pet. For cats and dogs.

Warnings

Shake well before use. Respect the dosage. Keep out of reach of children.

Direction

Start giving 1 spray a day for 10 days, in water or directly in the mouth. To maintain results: Continue giving 1 spray a day or bring down the dosage to 1 spray 1-3 times a week as needed. Please take note it usually takes about 5-10 days before seeing results.

Inactive ingredients

Ethyl alcohol 20%, purified water

Other information

The letters "HPUS" indicate that the active ingredients are in the official Homeopathic Pharmacopoeia of the United States. Homeopathic remedy. Store at room temperature.